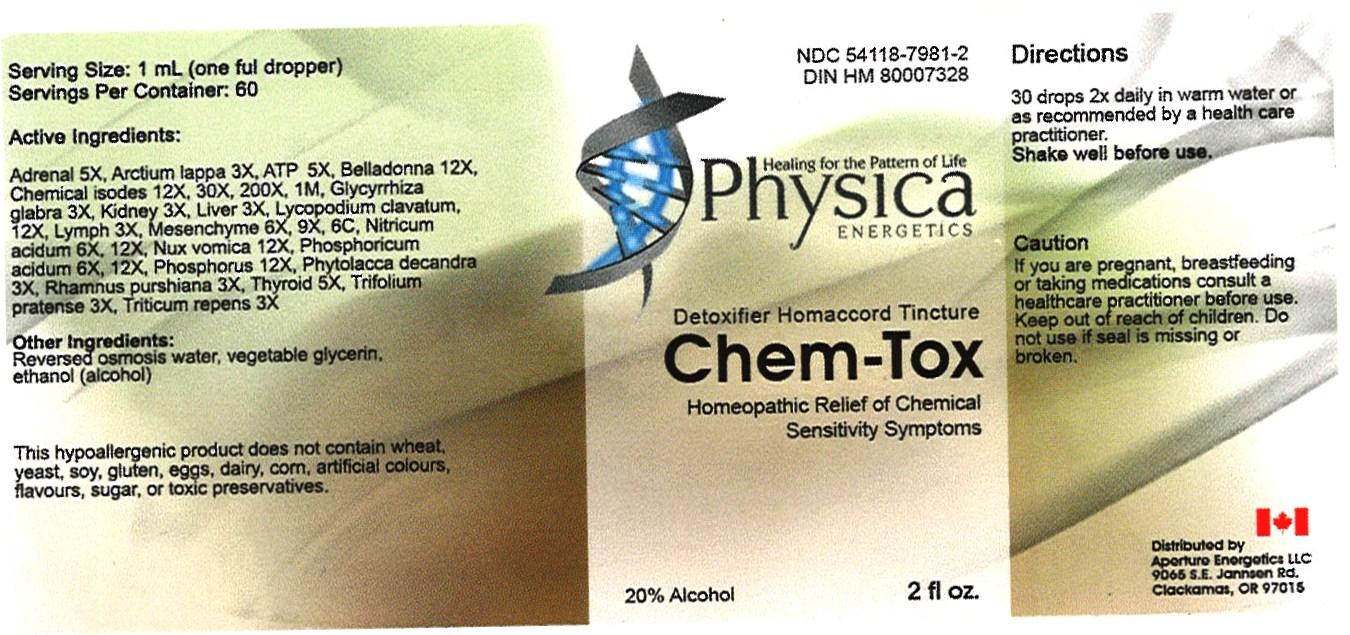 DRUG LABEL: Chem - Tox
NDC: 54118-7981 | Form: SOLUTION/ DROPS
Manufacturer: ABCO Laboratories, Inc.
Category: homeopathic | Type: HUMAN OTC DRUG LABEL
Date: 20121130

ACTIVE INGREDIENTS: BOS TAURUS ADRENAL GLAND 5 [hp_X]/60 mL; ARCTIUM LAPPA WHOLE 3 [hp_X]/60 mL; ADENOSINE TRIPHOSPHATE 5 [hp_X]/60 mL; ATROPA BELLADONNA 12 [hp_X]/60 mL; ARSENIC TRIOXIDE 12 [hp_X]/60 mL; LICORICE 3 [hp_X]/60 mL; BEEF KIDNEY 3 [hp_X]/60 mL; BEEF LIVER 3 [hp_X]/60 mL; LYCOPODIUM CLAVATUM SPORE 12 [hp_X]/60 mL; BOS TAURUS LYMPH 3 [hp_X]/60 mL; BOS TAURUS MESENCHYME 6 [hp_X]/60 mL; NITRIC ACID 6 [hp_X]/60 mL; STRYCHNOS NUX-VOMICA SEED 12 [hp_X]/60 mL; PHOSPHORIC ACID 6 [hp_X]/60 mL; PHOSPHORUS 12 [hp_X]/60 mL; PHYTOLACCA AMERICANA ROOT 3 [hp_X]/60 mL; FRANGULA PURSHIANA BARK 3 [hp_X]/60 mL; THYROID, BOVINE 5 [hp_X]/60 mL; TRIFOLIUM PRATENSE FLOWER 3 [hp_X]/60 mL; ELYMUS REPENS ROOT 3 [hp_X]/60 mL
INACTIVE INGREDIENTS: WATER; GLYCERIN; ALCOHOL

Chem-Tox

Active Ingredients:

- Adrenal 5x
- Arctium lappa 3x
- ATP 5x
- Belladonna 12x
- Chemical isodes 12X, 30x, 200x 1M
- Glycyrrhiza glabra 3x
- Kidney 3x
- Liver 3x
- Lycopodium clavatum 12x
- Lymph 3x
- Mesenchyme 6x, 9x, 6C
- Nitricum acidum 6x, 12x
- Nux vomica 12x
- Phosphoricum acidum 6x, 12x
- Phosphorus 12x
- Phytolacca decandra 3x
- Rhamnus purshiana 3x
- Thyroid 5x
- Trifolium pratense 3x
- Triticum repens 3x

PURPOSE

Detoxifier Homaccord Tincture
Homeopathic Relief of Chemical Hypersensitivity Symptoms

Keep out of reach of children

INDICATIONS AND USAGE

- 30 drops 2X daily in warm water
- or as recommended by a health care practitioner
- Shake Well before use

WARNINGS

If you are pregnant, breastfeeding or taking medications consult a health care practitioner before use.
Keep out of reach of children
Do not use if seal is missing or broken.

DOSAGE AND ADMINISTRATION

- 30 drops 2x daily in warm water
- or as recommended by a health care practitioner
- Shake well before use.

INACTIVE INGREDIENT

Reverse osmosis water
Vegetabe glycerin
Alcohol (ethanol)

PACKAGE LABEL

- chemtox.jpg
- image of bottle label